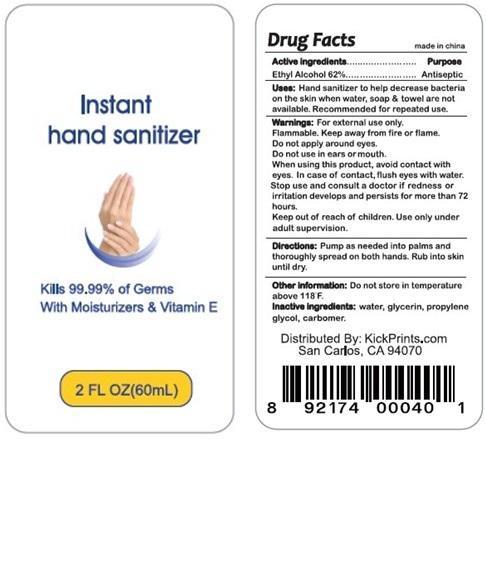 DRUG LABEL: Instant Hand Sanitizer KickPrints
                
NDC: 58948-1001 | Form: GEL
Manufacturer: Empire Stationery Distributors Inc.
Category: otc | Type: HUMAN OTC DRUG LABEL
Date: 20130618

ACTIVE INGREDIENTS: Alcohol 62 mL/100 mL
INACTIVE INGREDIENTS: WATER; GLYCERIN; PROPYLENE GLYCOL; CARBOMER HOMOPOLYMER TYPE C (ALLYL PENTAERYTHRITOL CROSSLINKED)

Active Ingredient

Ethyl Alcohol 62%

Purpose
Antiseptic

INDICATIONS AND USAGE

Kills 99.99% of Germs With Moisturizers & Vitamin E
Uses: Hand sanitizer to help decrease bacteria on the skin when water, soap & towel are not available. Recommended for repeated use.

WARNINGS

Warnings: For external use only. Flammable. Keep away from fire or flame.

Do not apply around eyes. Do not use in ears or mouth.
When using this product, avoid contact with eyes. In case of contact, flush eyes with water.

Stop use and consult a doctor if redness or irritation develops and persists for more than 72 hours.

Keep out of reach of children.

Use only under adult supervision.

DOSAGE AND ADMINISTRATION

Directions: Pump as needed into palms and thoroughly spread on both hands.

Rub into skin until dry.

Other information: Do not store in temperature above 118 F.

INACTIVE INGREDIENTS:

Water, Glycerin, Propylene Glycol, Carbomer